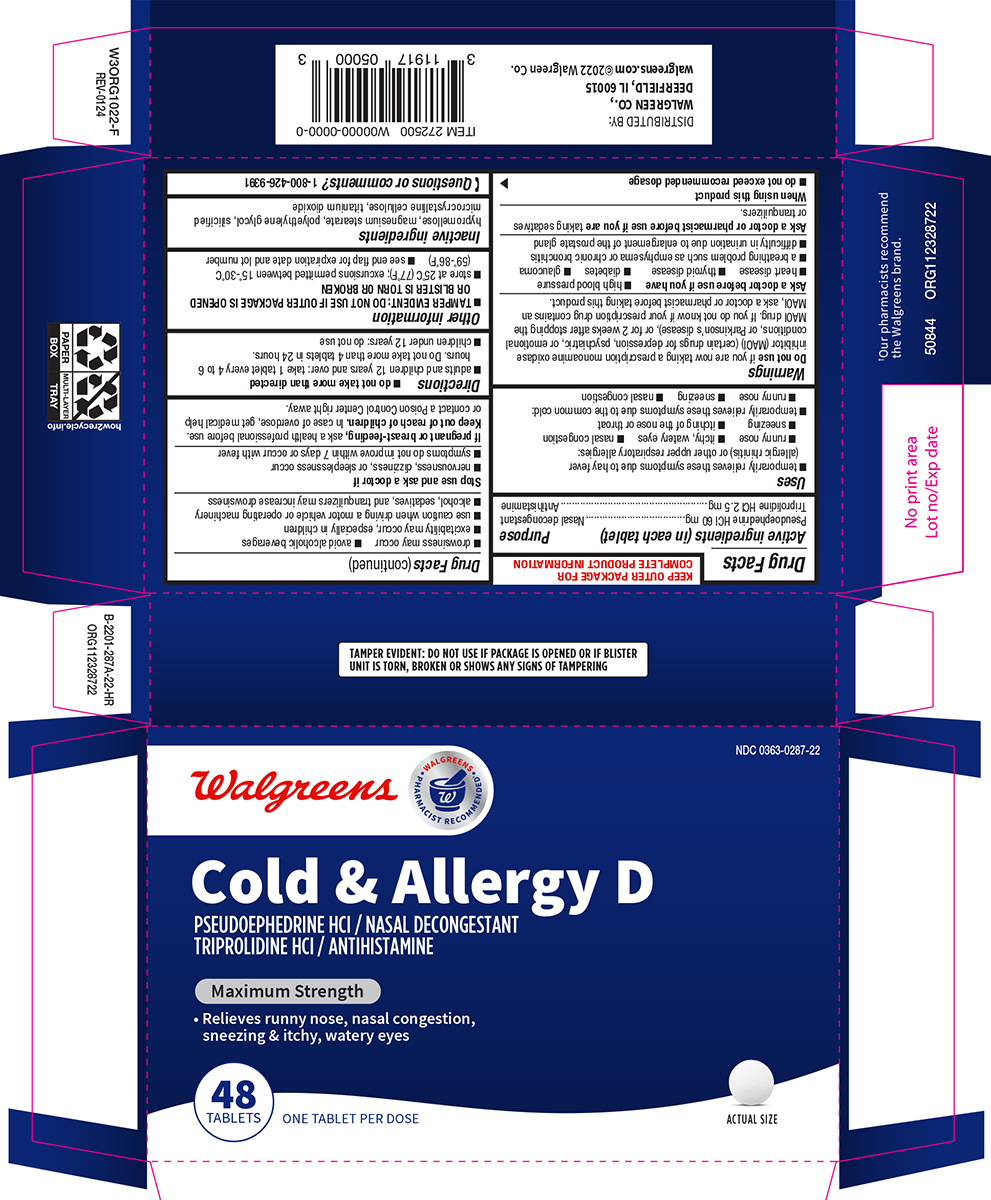 DRUG LABEL: Cold and Allergy D
NDC: 0363-0287 | Form: TABLET, FILM COATED
Manufacturer: Walgreen Company
Category: otc | Type: HUMAN OTC DRUG LABEL
Date: 20260203

ACTIVE INGREDIENTS: PSEUDOEPHEDRINE HYDROCHLORIDE 60 mg/1 1; TRIPROLIDINE HYDROCHLORIDE 2.5 mg/1 1
INACTIVE INGREDIENTS: HYPROMELLOSE, UNSPECIFIED; MAGNESIUM STEARATE; POLYETHYLENE GLYCOL, UNSPECIFIED; MICROCRYSTALLINE CELLULOSE; SILICON DIOXIDE; TITANIUM DIOXIDE

Walgreens 44-287

Active ingredients (in each tablet)

Pseudoephedrine HCl 60 mg
Triprolidine HCl 2.5 mg

Purpose

Nasal decongestant
Antihistamine

Uses

- temporarily relieves these symptoms due to hay fever (allergic rhinitis) or other upper respiratory allergies:
  - runny nose
  - itchy, watery eyes
  - nasal congestion
  - sneezing
  - itching of the nose or throat
- temporarily relieves these symptoms due to the common cold:
  - runny nose
  - sneezing
  - nasal congestion

Warnings

Do not use

if you are now taking a prescription monoamine oxidase inhibitor (MAOI) (certain drugs for depression, psychiatric, or emotional conditions, or Parkinson’s disease), or for 2 weeks after stopping the MAOI drug. If you do not know if your prescription drug contains an MAOI, ask a doctor or pharmacist before taking this product.

Ask a doctor before use if you have

- high blood pressure
- heart disease
- thyroid disease
- diabetes
- glaucoma
- a breathing problem such as emphysema or chronic bronchitis
- difficulty in urination due to enlargement of the prostate gland

Ask a doctor or pharmacist before use if you are

taking sedatives or tranquilizers.

When using this product

- do not exceed recommended dosage
- excitability may occur, especially in children
- use caution when driving a motor vehicle or operating machinery
- drowsiness may occur
- avoid alcoholic beverages
- alcohol, sedatives, and tranquilizers may increase drowsiness

Stop use and ask a doctor if

- nervousness, dizziness, or sleeplessness occur
- symptoms do not improve within 7 days or occur with fever

If pregnant or breast-feeding,

ask a health professional before use.

Keep out of reach of children.

In case of overdose, get medical help or contact a Poison Control Center right away.

Directions

- do not take more than directed
- adults and children 12 years and over: take 1 tablet every 4 to 6 hours. Do not take more than 4 tablets in 24 hours.
- children under 12 years: do not use

Other information

- TAMPER EVIDENT: DO NOT USE IF OUTER PACKAGE IS OPENED OR BLISTER IS TORN OR BROKEN
- store at 25°C (77°F); excursions permitted between 15°-30°C (59°-86°F)
- see end flap for expiration date and lot number

Inactive ingredients

hypromellose, magnesium stearate, polyethylene glycol, silicified microcrystalline cellulose, titanium dioxide

Questions or comments?

1-800-426-9391

Principal display panel

NDC 0363-0287-22

Walgreens
• WALGREENS •
PHARMACIST RECOMMENDED†

Cold & Allergy D
PSEUDOEPHEDRINE HCl / NASAL DECONGESTANT
TRIPROLIDINE HCl / ANTIHISTAMINE

Maximum Strength
• Relieves runny nose, nasal congestion,
sneezing & itchy, watery eyes

48
TABLETS
ONE TABLET PER DOSE
ACTUAL SIZE

TAMPER EVIDENT: DO NOT USE IF PACKAGE IS OPENED OR IF BLIS TER
UNIT IS TORN, BROKEN OR SHOWS ANY SIGNS OF TAMPERING

†Our pharmacists recommend
the Walgreens brand.
50844 ORG112328722
DISTRIBUTED BY:
WALGREEN CO.,
DEERFIELD, IL 60015
walgreens.com ©2022 Walgreen Co.

Walgreens 44-287A